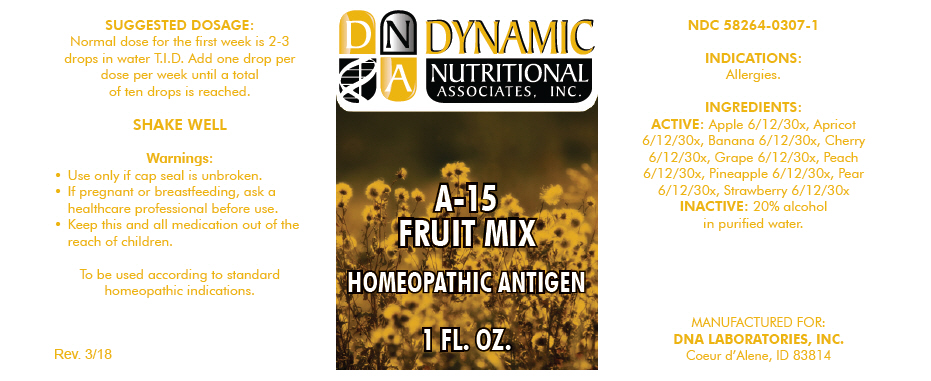 DRUG LABEL: A-15
NDC: 58264-0307 | Form: SOLUTION
Manufacturer: DNA Labs, Inc.
Category: homeopathic | Type: HUMAN OTC DRUG LABEL
Date: 20250109

ACTIVE INGREDIENTS: APPLE 30 [hp_X]/1 mL; APRICOT 30 [hp_X]/1 mL; BANANA 30 [hp_X]/1 mL; CHERRY 30 [hp_X]/1 mL; GRAPE 30 [hp_X]/1 mL; PEACH 30 [hp_X]/1 mL; PINEAPPLE 30 [hp_X]/1 mL; PEAR 30 [hp_X]/1 mL; STRAWBERRY 30 [hp_X]/1 mL
INACTIVE INGREDIENTS: WATER; ALCOHOL

A-15

NDC 58264-0307-1

INDICATIONS

PURPOSE

Allergies.

INGREDIENTS

ACTIVE

Apple 6/12/30x, Apricot 6/12/30x, Banana 6/12/30x, Cherry 6/12/30x, Grape 6/12/30x, Peach 6/12/30x, Pineapple 6/12/30x, Pear 6/12/30x, Strawberry 6/12/30x

INACTIVE

20% alcohol in purified water.

SUGGESTED DOSAGE

Normal dose for the first week is 2-3 drops in water T.I.D. Add one drop per dose per week until a total of ten drops is reached.

STORAGE AND HANDLING

SHAKE WELL

Warnings

- Use only if cap seal is unbroken.

PREGNANCY OR BREAST FEEDING

- If pregnant or breastfeeding, ask a healthcare professional before use.

KEEP OUT OF REACH OF CHILDREN

- Keep this and all medication out of the reach of children.

To be used according to standard homeopathic indications.

PRINCIPAL DISPLAY PANEL - 1 FL. OZ. Bottle Label

DYNAMIC
NUTRITIONAL
ASSOCIATES, INC.

A-15
FRUIT MIX

HOMEOPATHIC ANTIGEN

1 FL. OZ.